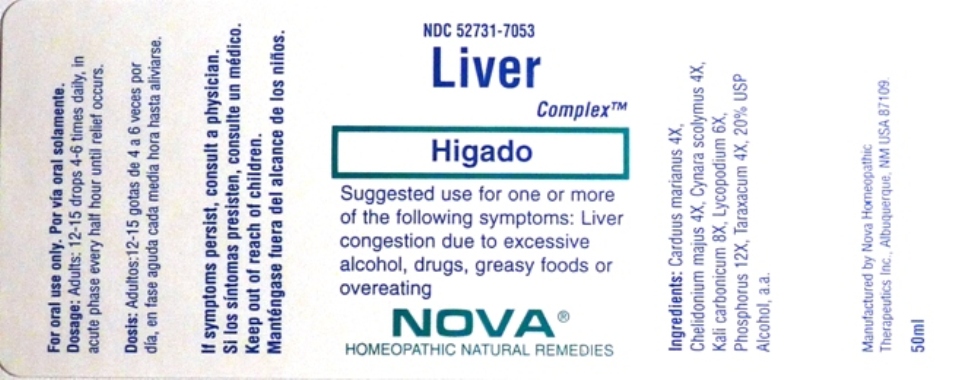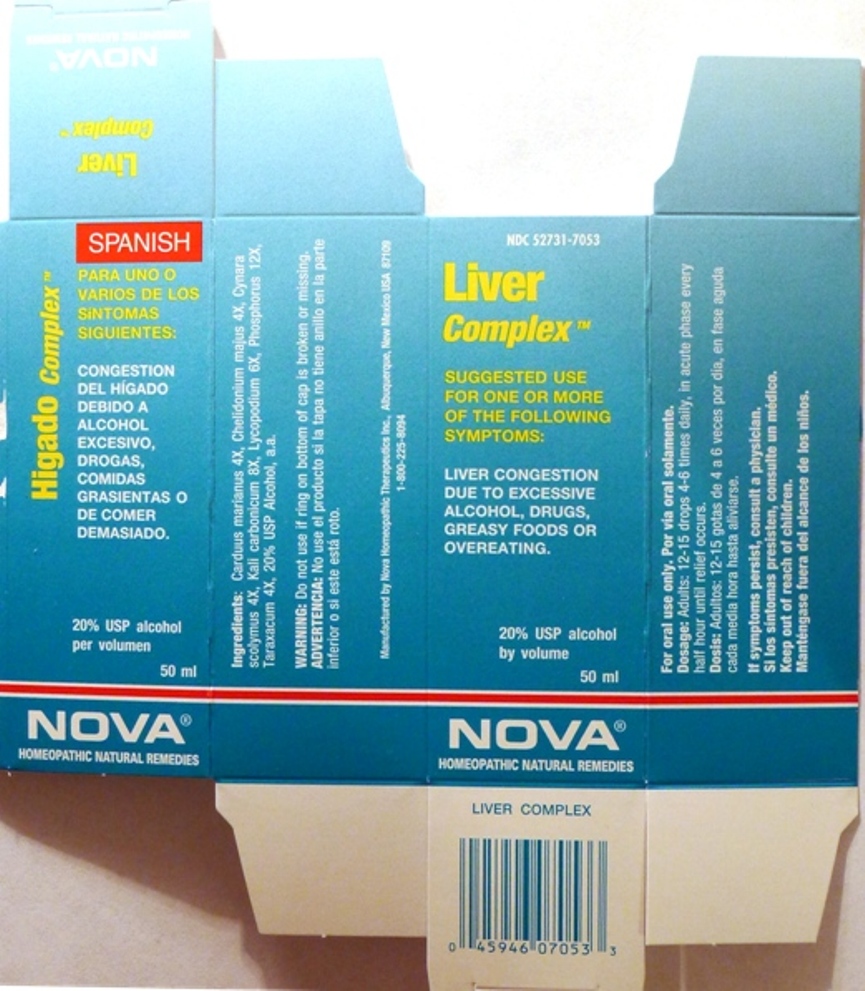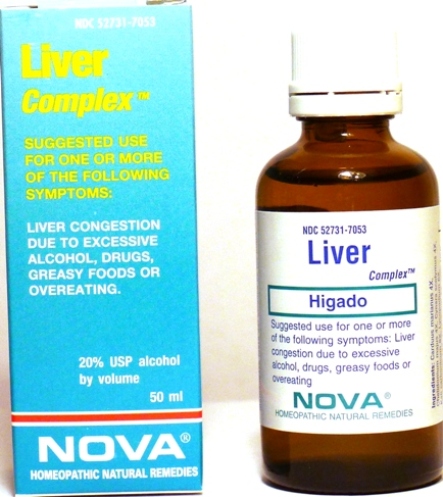 DRUG LABEL: Liver Complex
NDC: 52731-7053 | Form: LIQUID
Manufacturer: Nova Homeopathic Therapeutics, Inc.
Category: homeopathic | Type: HUMAN OTC DRUG LABEL
Date: 20110601

ACTIVE INGREDIENTS: SILYBUM MARIANUM SEED 4 [hp_X]/1 mL; CHELIDONIUM MAJUS 4 [hp_X]/1 mL; CYNARA SCOLYMUS LEAF 4 [hp_X]/1 mL; POTASSIUM CARBONATE 8 [hp_X]/1 mL; LYCOPODIUM CLAVATUM SPORE 6 [hp_X]/1 mL; PHOSPHORUS 12 [hp_X]/1 mL; TARAXACUM PALUSTRE ROOT 4 [hp_X]/1 mL
INACTIVE INGREDIENTS: ALCOHOL

Liver Complex

Purpose:

Suggested use for one or more of the following symptoms:

Liver congestion due to excessive alcohol, drugs, greasy foods or overeating.

Usage and Dosage:

For oral use only.

DOSAGE AND ADMINISTRATION

Adults:
In Acute Phase:
12-15 drops, every half hour until relief occurs
When Relief Occurs:
12-15 drops, 4-6 times per day

Warnings:

Keep out of reach of children.

WARNINGS

If symptoms persist, consult a physician.
Do not use if ring on bottom of cap is broken or missing.

Active Ingredients:

Carduus marianus 4X, Chelidonium majus 4X, Cynara scolymus 4X, Kali carbonicum 8X, Lycopodium 6X, Phosphorus 12X, Taraxacum 4X

Inactive Ingredients:

Alcohol, 20% USP

QUESTIONS

Manufactured by Nova Homeopathic Therapeutics Inc., Albuquerque, New Mexico USA 87109
1-800-225-8094

PACKAGE LABEL

Liver Complex Product

Liver Complex Bottle Label

Liver Complex Box